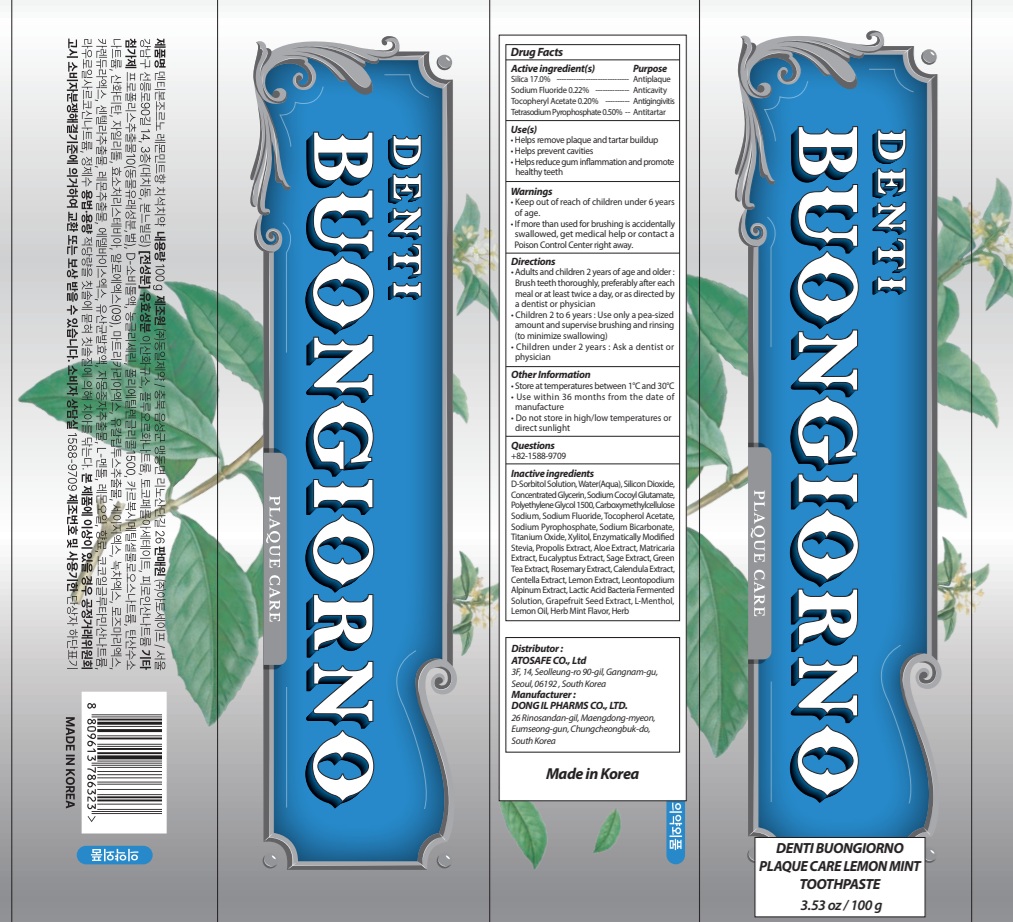 DRUG LABEL: DENTI BUONGIORNO PLAQUE CARE LEMON MINT TOOTH
NDC: 85601-090 | Form: PASTE, DENTIFRICE
Manufacturer: ATOSAFE CO., Ltd
Category: otc | Type: HUMAN OTC DRUG LABEL
Date: 20260116

ACTIVE INGREDIENTS: .ALPHA.-TOCOPHEROL ACETATE 0.2 g/100 g; SODIUM PYROPHOSPHATE 0.5 g/100 g; SILICON DIOXIDE 17 g/100 g; SODIUM FLUORIDE 0.22 g/100 g
INACTIVE INGREDIENTS: SORBITOL; WATER; GLYCERIN

Active ingredient(s)

Silica 17.0%
Sodium Fluoride 0.22%
Tocopheryl Acetate 0.20%
Tetrasodium Pyrophosphate 0.50%

Purpose

Antiplaque, Anticavity, Antigingivitis, Antitartar

Warnings

• Keep out of reach of children under 6 years of age.
• If more than used for brushing is accidentally swallowed, get medical help or contact a Poison Control Center right away.

KEEP OUT OF REACH OF CHILDREN

Keep out of reach of childrenunder 6 years of age.

INDICATIONS AND USAGE

Use(s)

• Helps remove plaque and tartar buildup
• Helps prevent cavities
• Helps reduce gum inflammation and promote healthy teeth

Directions

• Adults and children 2 years of age and older : Brush teeth thoroughly, preferably after each meal or at least twice a day, or as directed by a dentist or physician

• Children 2 to 6 years : Use only a pea sized amount and supervise child's brushing and rinsing (to minimize swallowing)

• Children under 2 years : Ask a dentist or physician

Other Information

• Store at temperatures between 1°C and 30°C
• Use within 36 months from the date of manufacture
• Do not store in high/low temperatures or direct sunlight

Questions

+82-1588-9709

Inactive ingredients

D-Sorbitol Solution, Water(Aqua), Silicon Dioxide, Concentrated Glycerin, Sodium Cocoyl Glutamate, Polyethylene Glycol 1500, Carboxymethylcellulose Sodium, Sodium Fluoride, Tocopherol Acetate, Sodium Pyrophosphate, Sodium Bicarbonate, Titanium Oxide, Xylitol, Enzymatically Modified Stevia, Propolis Extract, Aloe Extract, Matricaria Extract, Eucalyptus Extract, Sage Extract, Green Tea Extract, Rosemary Extract, Calendula Extract, Centella Extract, Lemon Extract, Leontopodium Alpinum Extract, Lactic Acid Bacteria Fermented Solution, Grapefruit Seed Extract, L-Menthol, Lemon Oil, Herb Mint Flavor, Herb